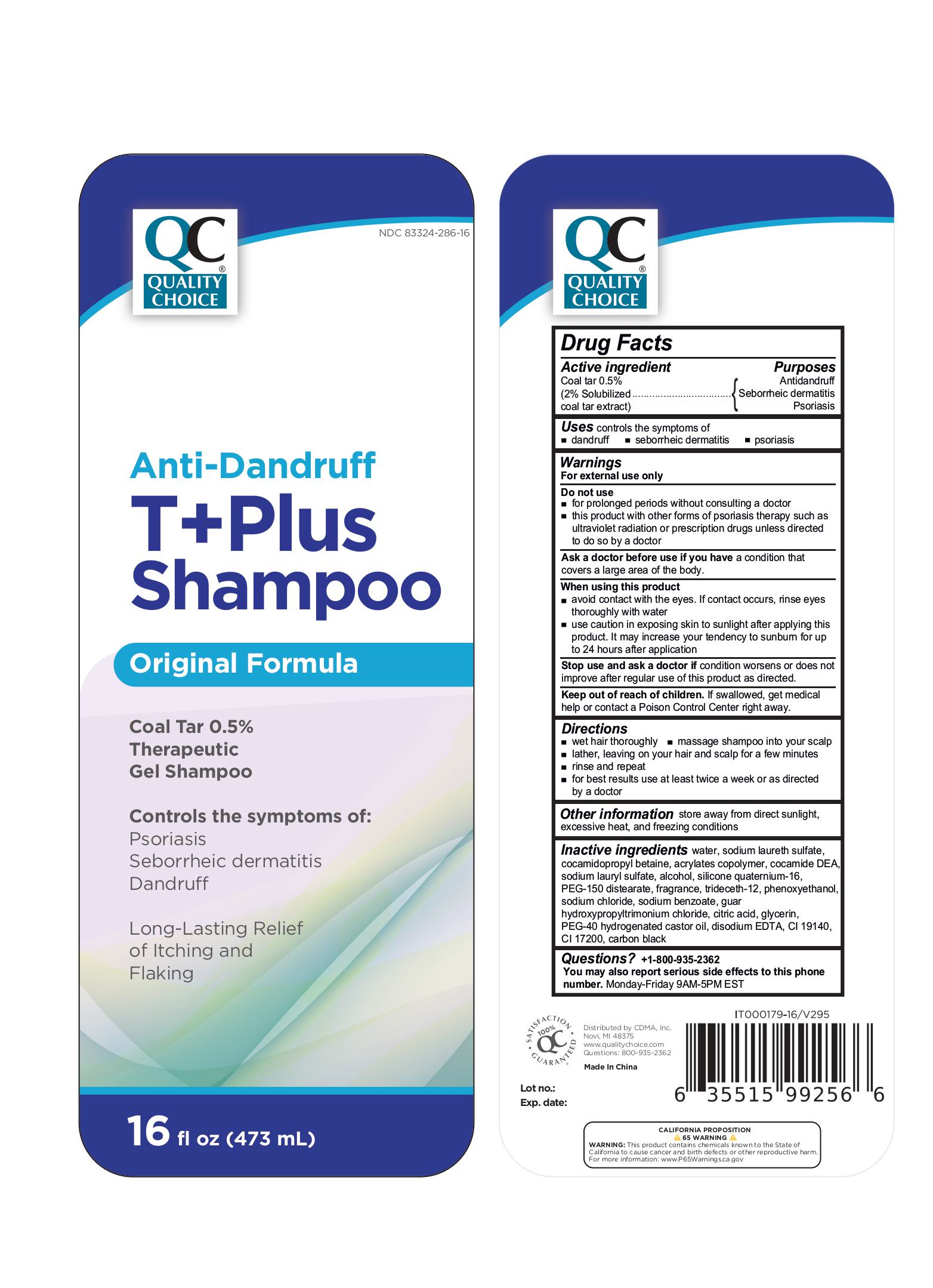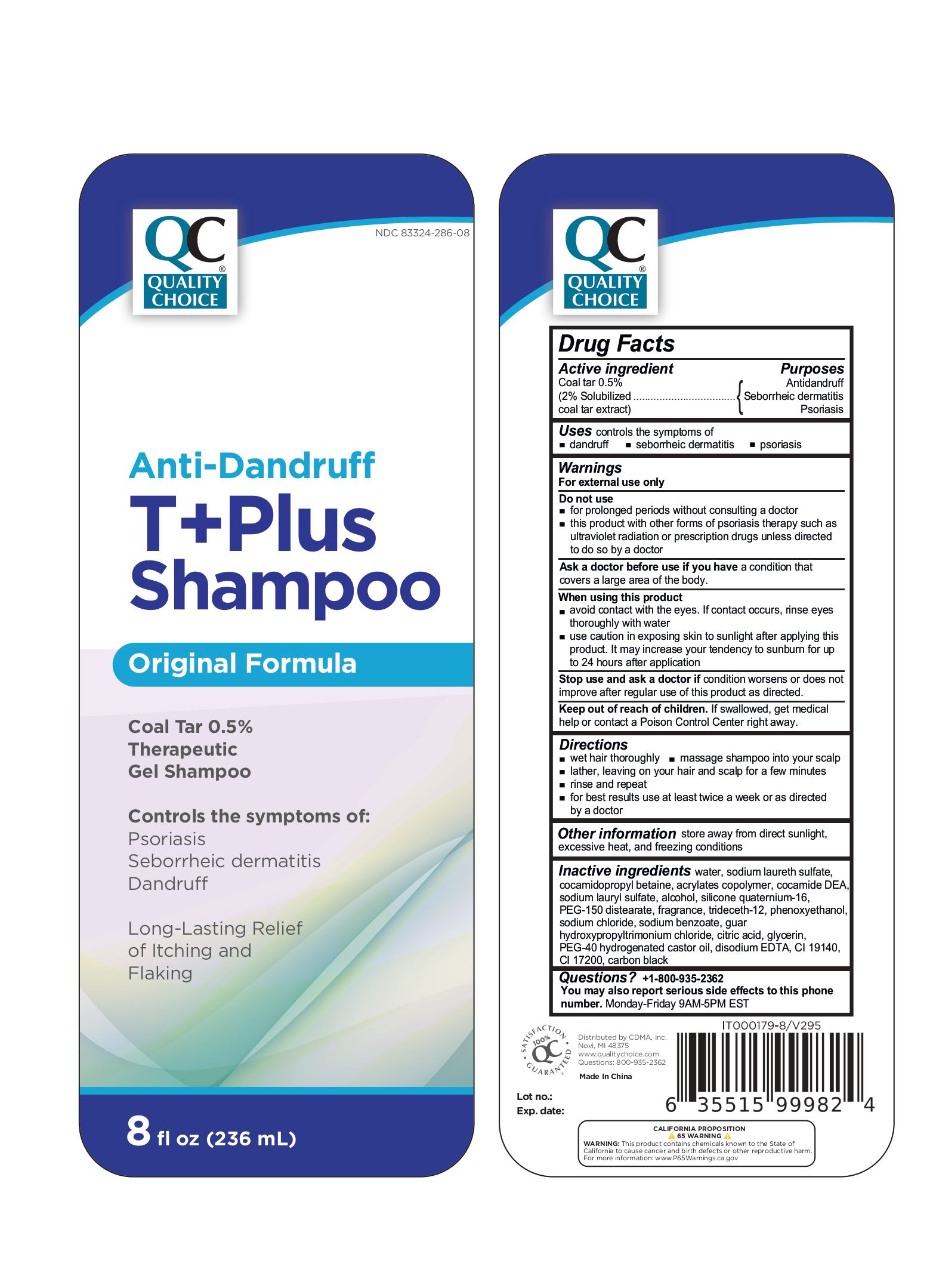 DRUG LABEL: QC Anti Dandruff T Plus
NDC: 75376-286 | Form: LOTION/SHAMPOO
Manufacturer: Guangzhou Danting Bath&Body Care Industry Co. Ltd.
Category: otc | Type: HUMAN OTC DRUG LABEL
Date: 20250124

ACTIVE INGREDIENTS: COAL TAR 5 mg/1 mL
INACTIVE INGREDIENTS: SODIUM LAURETH SULFATE; BUTYL ACRYLATE/METHYL METHACRYLATE/METHACRYLIC ACID COPOLYMER (18000 MW); COCAMIDE DEA; SODIUM BENZOATE; WATER; TRIDECETH-12; PHENOXYETHANOL; CITRIC ACID; PEG-40 HYDROGENATED CASTOR OIL; EDETATE DISODIUM; CI 17200; CARBON BLACK; SODIUM CHLORIDE; PEG-150 DISTEARATE; SODIUM LAURYL SULFATE; ALCOHOL; CI 19140; GUAR HYDROXYPROPYLTRIMONIUM CHLORIDE; QUATERNIUM-16; GLYCERIN; COCAMIDOPROPYL BETAINE

QC T PLUS 0.5%

Drug Facts

Active ingredient

Coal tar 0.5% (2% solubilized coal tar extract)

Purposes

Antidandruff, Seborrhic dematitis, Psoriasis

Uses

Controls the symptoms of

- dandruf
- seborrheic dermatitis
- psoriasis

Warnings

For external use only

Do not use

- for prolonged periods without consulting a doctor
- this product with other forms of psoriasis therapy such as ultraviolet radiation or prescription drugs unless directed to do so by a doctor

Ask a doctor before use if you have

a condition that covers a large area of the body

When using this product

- avoid contact with the eyes. If contact occurs, rinse eyes thoroughly with water
- use caution in exposing skin to sunlight after applying this product. It may increase your tendency to sunburn for up to 24 hours after application

Stop use and ask a doctor if

condition worsens or does not improve after regular use of this product as directed

Keep out of reach of children

If swallowed, get medical help or contact a Poison Control Center right away.

Directions

- wet hair thoroughly
- massage shampoo into your scalp
- lather, leaving on your hair and scalp for a few minutes
- rinse and repeat
- for best results use at least twice a week or as directed by a doctor

Other information

store away from direct sunlight, excessive heat, and freezing conditions

Inactive ingedients

water, sodium laureth sulfate, cocamidopropyl betaine, acrylates copolymer, cocamide DEA, sodium lauryl sulfate, alcohol, silicone quaternium-16, PEG-150 distearate, fragrance, trideceth-12, phenoxyethanol, sodium chloride, sodium benzoate, guar hydroxypropyltrimonium chloride, citric acid, glycerin, PEG-40 hydrogenated castor oil, disodium EDTA, CI 19140, CI 17200, carbon black

Questions?

+1-800-935-2362
You may also report serious side effects to this phone
number. Monday-Friday 9AM-5PM EST